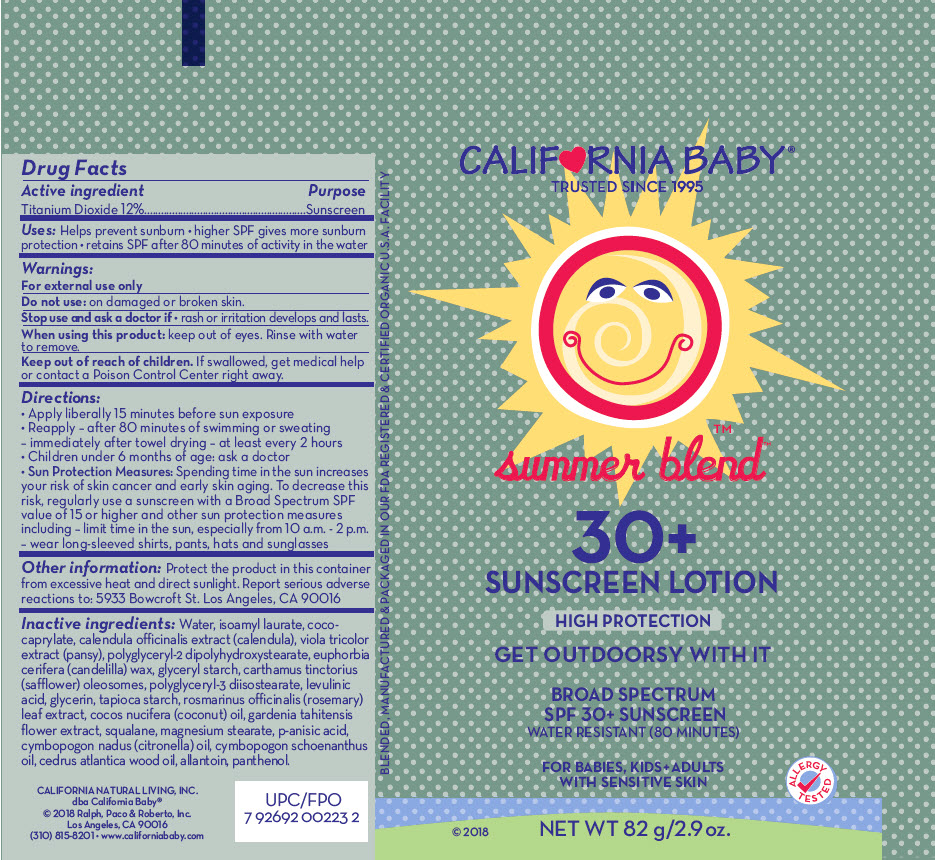 DRUG LABEL: SPF30 SUMMER BLEND SUNSCREEN
NDC: 52915-040 | Form: LOTION/SHAMPOO
Manufacturer: ORGANIC & SUSTAINABLE BEAUTY
Category: otc | Type: HUMAN OTC DRUG LABEL
Date: 20241107

ACTIVE INGREDIENTS: TITANIUM DIOXIDE 120 mg/1 g
INACTIVE INGREDIENTS: Water; alkyl (c12-15) benzoate; carthamus tinctorius seed oleosomes; coco-caprylate; glycerin; polyhydroxystearic acid (2300 MW); medium-chain triglycerides; polyglyceryl-2 dipolyhydroxystearate; candelilla wax; coconut oil; starch, tapioca; polyglyceryl-3 diisostearate; rosemary; squalane; allantoin; panthenol; magnesium stearate; levulinic acid; citronella oil; cymbopogon schoenanthus oil; cedrus atlantica bark oil; caprylhydroxamic acid; GLYCERYL MONOCAPRYLATE

SPF30+ SUMMER BLEND™ SUNSCREEN LOTION

Drug Facts

Active ingredient

Titanium Dioxide 12%

Purpose

Sunscreen

Uses

- helps prevent sunburn

Warnings

For external use only.

Do not use on damaged or broken skin.

Stop use and ask a doctor if rash occurs.

When using this product keep out of eyes. Rinse with water to remove.

Keep out of reach of children. If swallowed, get medical help or contact a Poison Control Center right away.

Directions

- Apply liberally 30 minutes before sun exposure
- Reapply – after 80 minutes of swimming or sweating immediately after towel drying – at least every 2 hours
- Children under 6 months: ask a doctor
- Sun Protection Measures: Spending time in the sun increases your risk of skin cancer and early skin aging. To decrease this risk, regularly use a sunscreen with a Broad Spectrum SPF value of 15 or higher and other sun protection measures including – limit time in the sun, especially from 10 a.m. - 2 p.m. – wear long-sleeved shirts, pants, hats and sunglasses

Other information

- protect the product in this container from excessive heat and direct sunlight
- report serious adverse reactions to: 5933 Bowcroft St. Los Angeles, CA 90016

Inactive ingredients

Water, c12-15 alkyl benzoate, coco-caprylate, glycerin, polyhydroxystearic acid, caprylic/capric triglyceride, polyglyceryl-2 dipolyhydroxystearate, candelilla cera, cocos nucifera (coconut) oil, tapioca starch, polyglyceryl-3 diisostearate, rosmarinus officinalis (rosemary) leaf extract, squalane, allantoin, panthenol, magnesium stearate, sodium levulinate, cymbopogon nardus oil, cymbopogon schoenanthus oil, cedrus atlantica wood oil, caprylhydroxamic acid, glyceryl caprylate.

PRINCIPAL DISPLAY PANEL - 82 g Tube Label

CALIFORNIA BABY®
TRUSTED SINCE 1995

summer blend™

30+
SUNSCREEN LOTION

HIGH PROTECTION

GET OUTDOORSY WITH IT

BROAD SPECTRUM
SPF 30+ SUNSCREEN
WATER RESISTANT (80 MINUTES)

FOR BABIES, KIDS + ADULTS
WITH SENSITIVE SKIN

ALLERGY
TESTED

© 2018
NET WT 82 g/2.9 oz.

BLENDED, MANUFACTURED & PACKAGED IN OUR FDA REGISTERED & CERTIFIED ORGANIC U.S.A. FACILITY